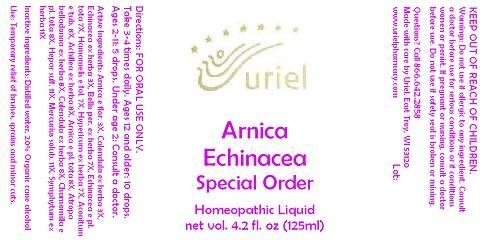 DRUG LABEL: Arnica Echinacea Special Order
NDC: 48951-1258 | Form: LIQUID
Manufacturer: Uriel Pharmacy Inc.
Category: homeopathic | Type: HUMAN OTC DRUG LABEL
Date: 20141125

ACTIVE INGREDIENTS: ARNICA MONTANA FLOWER 3 [hp_X]/1 mL; CALENDULA OFFICINALIS FLOWERING TOP 3 [hp_X]/1 mL; ECHINACEA ANGUSTIFOLIA 3 [hp_X]/1 mL; BELLIS PERENNIS 7 [hp_X]/1 mL; ECHINACEA, UNSPECIFIED 7 [hp_X]/1 mL; HAMAMELIS VIRGINIANA LEAF 7 [hp_X]/1 mL; ST. JOHN'S WORT 7 [hp_X]/1 mL; ACONITUM NAPELLUS 8 [hp_X]/1 mL; ACHILLEA MILLEFOLIUM 8 [hp_X]/1 mL; ARNICA MONTANA 8 [hp_X]/1 mL; ATROPA BELLADONNA 8 [hp_X]/1 mL; MATRICARIA RECUTITA 8 [hp_X]/1 mL; CALCIUM SULFIDE 11 [hp_X]/1 mL; MERCURIUS SOLUBILIS 11 [hp_X]/1 mL; COMFREY ROOT 11 [hp_X]/1 mL
INACTIVE INGREDIENTS: WATER; ALCOHOL

Arnica Echinacea Special Order

INDICATIONS AND USAGE

Directions: FOR ORAL USE ONLY.

DOSAGE AND ADMINISTRATION

Take 3-4 times daily. Ages 12 and older: 10 drops. Ages 2-11: 5 drops. Under age 2: Consult a doctor.

ACTIVE INGREDIENT

Active Ingredients: Arnica e flor. 3X, Calendula ex herba 3X, Echinacea ex herba 3X, Bellis per. ex herba 7X, Echinacea e pl. tota 7X, Hamamelis e fol. 7X, Hypericum ex herba 7X, Aconitum e tub. 8X, Achillea ex herba 8X, Arnica e pl. tota 8X, Atropa belladonna ex herba 8X, Calendula ex herba 8X, Chamomilla e pl. tota 8X, Hepar sulf. 11X, Mercurius solub. 11X, Symphytum ex herba 11X

Inactive Ingredients: Distilled water, 20% Organic cane alcohol

PURPOSE

Use: Temporary relief of bruises, sprains and minor cuts.

KEEP OUT OF REACH OF CHILDREN.

WARNINGS

Warnings: Do not use if allergic to any ingredient. Consult a doctor before use for serious conditions or if conditions worsen or persist. If pregnant or nursing, consult a doctor before use. Do not use if safety seal is broken or missing.

QUESTIONS

Questions? Call 866.642.2858 Made with care by Uriel, East Troy, WI 53120 www.urielpharmacy.com